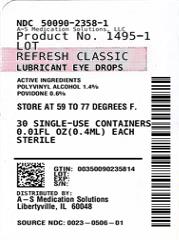 DRUG LABEL: REFRESH CLASSIC
NDC: 50090-2358 | Form: SOLUTION/ DROPS
Manufacturer: A-S Medication Solutions
Category: otc | Type: HUMAN OTC DRUG LABEL
Date: 20240314

ACTIVE INGREDIENTS: POLYVINYL ALCOHOL 14 mg/1 mL; POVIDONE 6 mg/1 mL
INACTIVE INGREDIENTS: water; sodium chloride; hydrochloric acid; sodium hydroxide

REFRESH CLASSIC

Active ingredients

Polyvinyl Alcohol 1.4%

Povidone 0.6%

Purpose

Eye lubricant

Eye lubricant

Uses

- For the temporary relief of burning, irritation, and discomfort due to dryness of the eye or exposure to wind or sun.
- May be used as a protectant against further irritation.

Warnings

- For external use only.
- To avoid contamination, do not touch tip of container to any surface. Do not reuse. Once opened, discard.
- Do not touch unit-dose tip to eye.
- If solution changes color or becomes cloudy, do not use.

Stop use and ask a doctor if

you experience eye pain, changes in vision, continued redness or irritation of the eye, or if the condition worsens or persists for more than 72 hours.

Keep out of reach of children.

If swallowed, get medical help or contact a Poison Control Center right away.

Directions

To open, TWIST AND PULL TAB TO REMOVE. Instill 1 or 2 drops in the affected eye(s) as needed and discard container.

Other information

- Use only if single-use container is intact.
- Use before expiration date marked on container.
- Store at 59°-77°F (15°-25°C).
- RETAIN THIS CARTON FOR FUTURE REFERENCE.

Inactive ingredients

Purified water and sodium chloride. May also contain hydrochloric acid and/or sodium hydroxide (to adjust pH).

Questions or comments?

1.800.678.1605

refreshbrand.com

v1.0DFL0506

HOW SUPPLIED

Product: 50090-2358

NDC: 50090-2358-1 .4 mL in a VIAL, SINGLE-USE / 30 in a CARTON